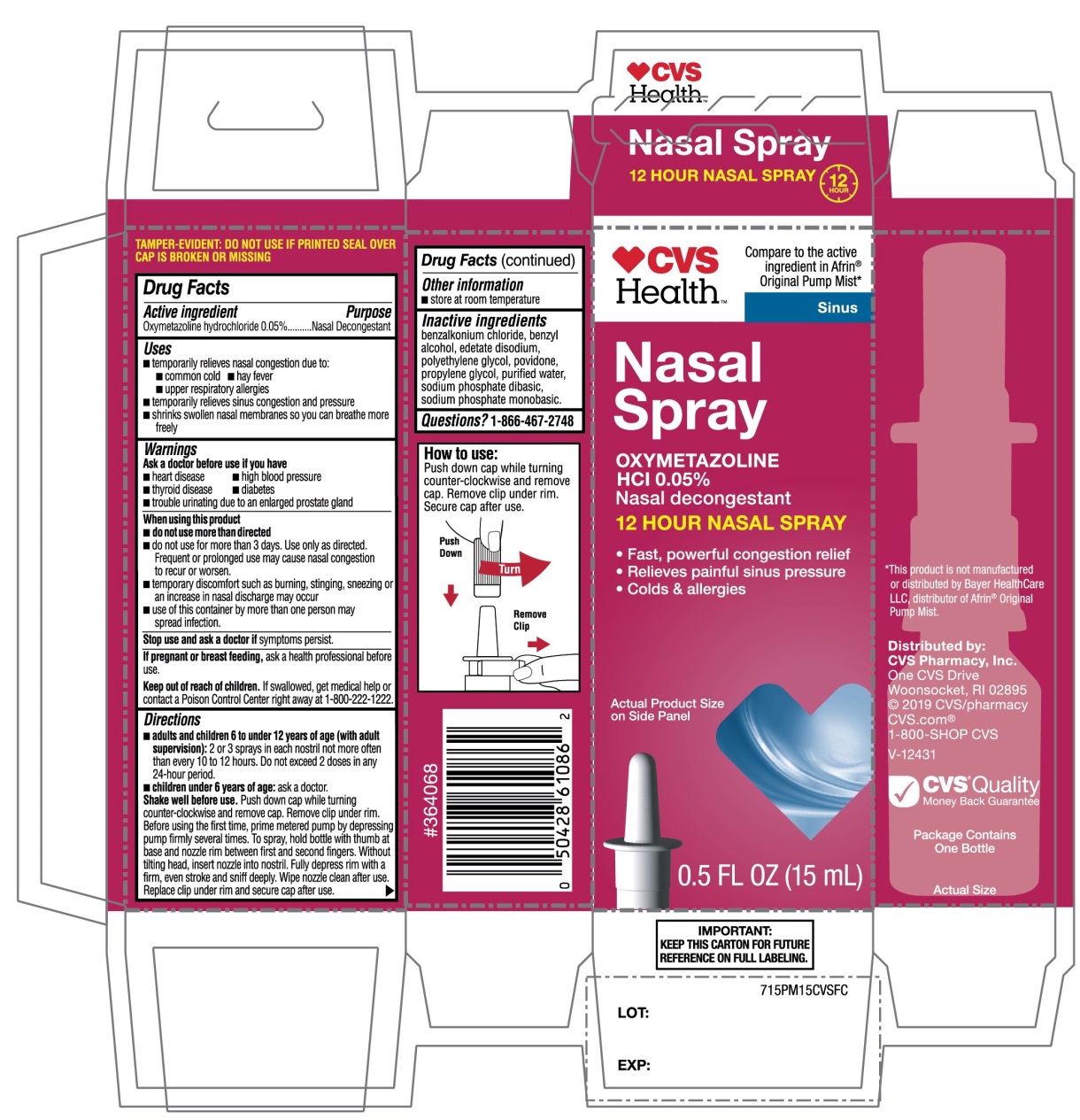 DRUG LABEL: CVS Health

NDC: 69842-715 | Form: SPRAY
Manufacturer: CVS PHARMACY, INC.
Category: otc | Type: HUMAN OTC DRUG LABEL
Date: 20251209

ACTIVE INGREDIENTS: OXYMETAZOLINE HYDROCHLORIDE 0.05 g/100 mL
INACTIVE INGREDIENTS: BENZALKONIUM CHLORIDE; BENZYL ALCOHOL; EDETATE DISODIUM; POLYETHYLENE GLYCOL, UNSPECIFIED; POVIDONE, UNSPECIFIED; PROPYLENE GLYCOL; WATER; SODIUM PHOSPHATE, DIBASIC, UNSPECIFIED FORM; SODIUM PHOSPHATE, MONOBASIC, UNSPECIFIED FORM

CVS Health™Nasal Oxymetazoline Spray Drug Facts

Active ingredient

Oxymetazoline hydrochloride 0.05%

Purpose

Nasal Decongestant

Uses

- temporarily relief of nasal congestion due to the
- common cold
- hay fever
- upper respiratory allergies
- temporarily relieves sinus congestion and pressure
- shrinks swollen nasal membranes so you can breathe more freely

Ask a doctor before use if you have

- heart disease
- high blood pressure
- diabetes
- thyroid disease
- trouble urinating due to an enlarged prostate gland

When using this product

- do not use more than directed
- do not use for more than 3 days. Use only as directed. Frequent or prolonged use may cause nasal congestion to recur or worsen.
- temporary discomfort such as burning, stinging, sneezing or an increase in nasal discharge may occur
- use of this container by more than one person may spread infection

Stop use and ask a doctor if

symptoms persist

If pregnant or breast-feeding,

ask a health professional before use.

Keep out of reach of children.

If swallowed, get medical help or contact a Poison Control Center right away at (1-800-222-1222).

Directions

- adults and children 6 to under 12 years of age (with adult supervision):2 or 3 sprays in each nostril not more often than every 10 to 12 hours. Do not exceed 2 doses in any 24-hour period.
- children under 6 years of age:ask a doctor

Shake well before use.Push down cap while turning counter-clockwise and remove cap .Remove clip under rim. Before using the first time, prime metered pump by depressing pump firmly several times. To spray, hold bottle with thumb at base and nozzle between first and second fingers without titling head, insert nozzle into nostril. Fully depress rim with a firm, even stroke and sniff deeply. Wipe nozzle clean after use. Replace clip under rim and secure cap after use.

Other information

- store at room temperature

Inactive ingredients

benzalkonium chloride, benzyl alcohol, edetate disodium, polyethylene glycol, povidone, propylene glycol, purified water, sodium phosphate dibasic, sodium phosphate monobasic.

Questions or comments?

1-866-467-2748

Principal Display Panel

CVS Health™

NDC# 69842-715-15

Compare to the active ingredient in AFRIN® Original Pump Mist*

Sinus

Nasal Spray

OXYMETAZOLINE HCl 0.05%

Nasal Decongestant

12 HOUR NASAL SPRAY

- Fast, powerful congestion relief
- Relieves painful sinus pressure
- Cold & allergies

0.5 FL OZ (15 mL)

IMPORTANT: KEEP THE CARTON FOR FUTURE REFERENCE ON FULL LABELING

Distributed by:

CVS Pharmacy, Inc.

One CVS Drive, Woonsocket, RI 02895

2019 CVS/pharmacy

CVS.com

1-800-SHOP CVS, V-12431

- CVS Quality
  Money Back Guarantee

*This product is not manufactured or distributed by Bayer Healthcare LLC, distributer of Afrin®Original Pump Mist.